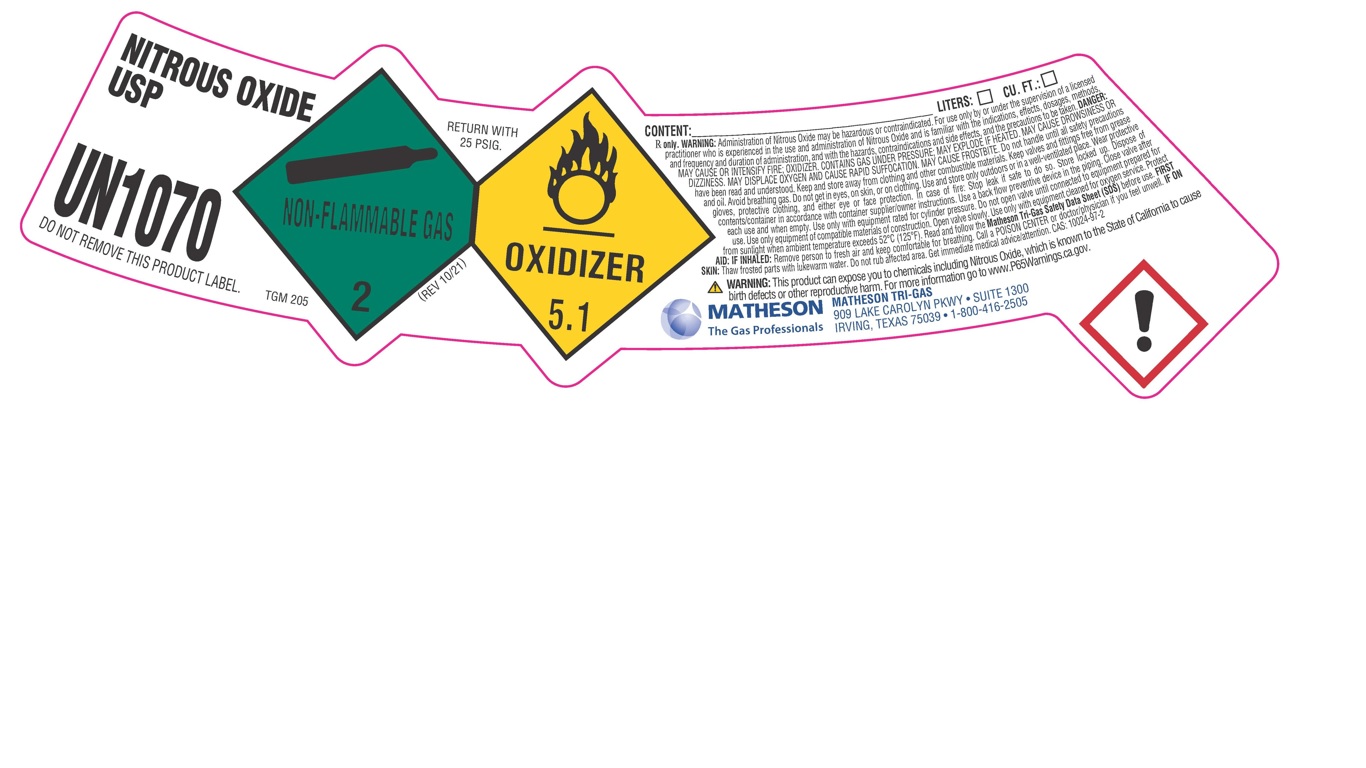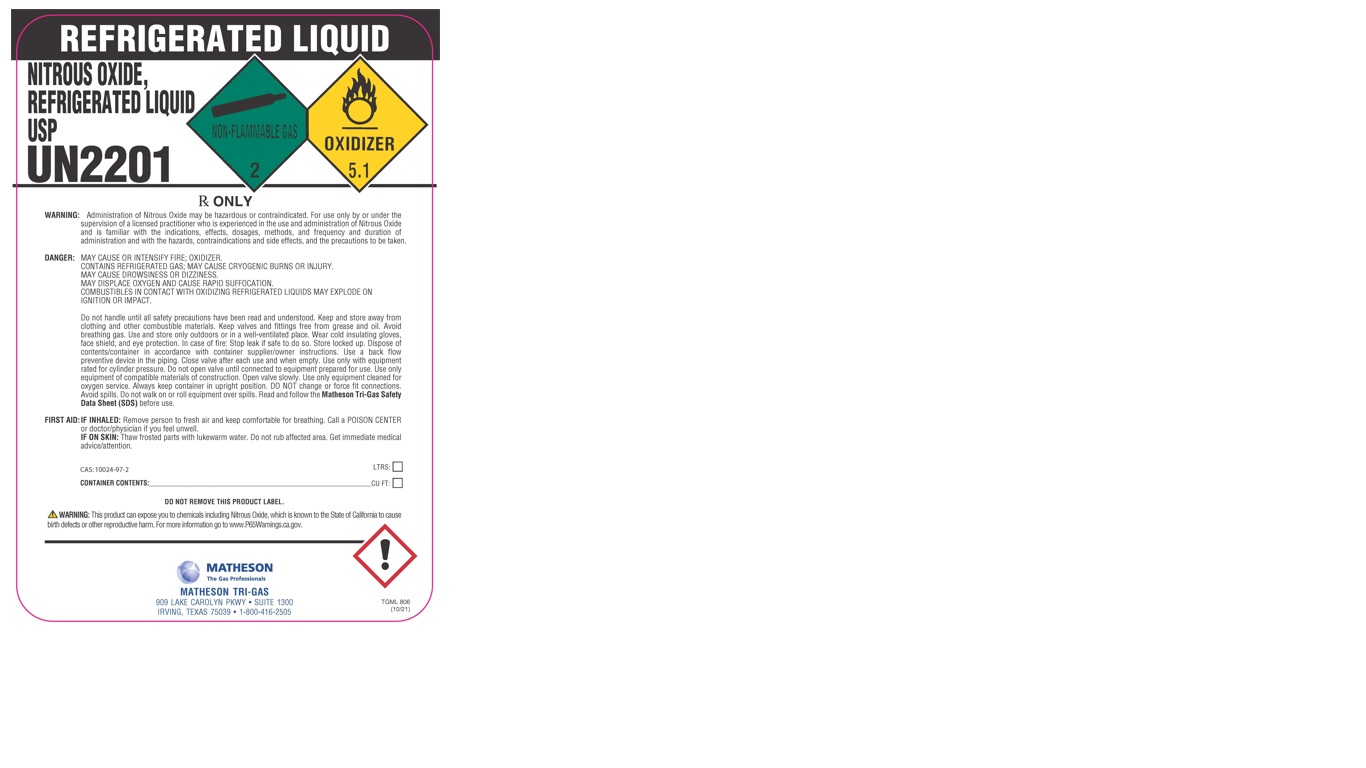 DRUG LABEL: Nitrous Oxide
NDC: 55037-301 | Form: GAS
Manufacturer: Matheson Tri-Gas, Inc.
Category: prescription | Type: HUMAN PRESCRIPTION DRUG LABEL
Date: 20251202

ACTIVE INGREDIENTS: NITROUS OXIDE 992 mL/1 L

nitrous oxide

PACKAGE LABEL

NITROUS OXIDE USP

UN1070

DO NOT REMOVE THIS PRODUCT LABEL.

CONTENT: LITERS: CU. FT.:

Rx only. WARNING: Administration of Nitrous Oxide may be hazardous or contraindicated. For use only by or under the supervision of a licensed practitioner who is experienced in the use and administration of Nitrous Oxide and is familiar with the indications, effects, dosages, methods, and frequency and duration of administration, and with the hazards, contraindications and side effects, and the precautions to be taken. DANGER: MAY CAUSE OR INTENSIFY FIRE; OXIDIZER. CONTAINS GAS UNDER PRESSURE; MAY EXPLODE IF HEATED. MAY CAUSE DROWSINESS OR DIZZINESS. MAY DISPLACE OXYGEN AND CAUSE RAPID SUFFOCATION. MAY CAUSE FROSTBITE. Do not handle until all safety precautions have been read and understood. Keep and store away from clothing and other combustible materials. Keep valves and fittings free from grease and oil. Avoid breathing gas. Do not get in eyes, on skin, or on clothing. Use and store only outdoors or in a well-ventilated place. Wear protective gloves, protective clothing, and either eye or face protection. In case of fire: Stop leak if safe to do so. Store locked up. Dispose of contents/container in accordance with container supplier/owner instructions. Use a back flow preventive device in the piping. Close valve after each use and when empty. Use only with equipment rated for cylinder pressure. Do not open valve until connected to equipment prepared for use. Use only equipment of compatible materials of construction. Open valve slowly. Use only with equipment cleaned for oxygen service. Protect from sunlight when ambient temperature exceeds 52 C (125 F). Read and follow the Matheson Tri-Gas Safety Data Sheet (SDS) before use. FIRST AID: IF INHALED: Remove person to fresh air and keep comfortable for breathing. Call a POISON CENTER or doctor/physician if you feel unwell. IF ON SKIN: Thaw frosted parts with lukewarm water. Do not rub affected area. Get immediate medical advice/attention. CAS: 10024-97-2

WARNING: This product can expose you to chemicals including Nitrous Oxide, which is known to the State of California to cause birth defects or other reproductive harm. For more information go to www.P65Warnings.ca.gov.

MATHESON The Gas Professionals

MATHESON TRI-GAS

909 LAKE CAROLYN PKWY. SUITE 1300

IRVING, TEXAS 75039 . 1-800-416-2505

PACKAGE LABEL

REFRIGERATED LIQUID

NITROUS OXIDE, REFRIGERATED LIQUID USP

UN2201

Rx ONLY

WARNING: Administration of Nitrous Oxide may be hazardous or contraindicated. For use only by or under the supervision of a licensed practitioner who is experienced in the use and administration of Nitrous Oxide and is familiar with the indications, effects, dosages, methods, and frequency and duration of administration and with the hazards, contraindications and side effects, and the precautions to be taken.

DANGER: MAY CAUSE OR INTENSIFY FIRE; OXIDIZER. CONTAINS REFRIGERATED GAS; MAY CAUSE CRYOGENIC BURNS OR INJURY. MAY CAUSE DROWSINESS OR DIZZINESS. MAY DISPLACE OXYGEN AND CAUSE RAPID SUFFOCATION. COMBUSTIBLES IN CONTACT WITH OXIDIZING REFRIGERATED LIQUIDS MAY EXPLODE ON IGNITION OR IMPACT.

Do not handle until all safety precautions have been read and understood. Keep and store away from clothing and other combustible materials. Keep valves and fittings free from grease and oil. Avoid breathing gas. Use and store only outdoors or in a well-ventilated place. Wear cold insulating gloves, face shield, and eye protection. In case of fire: Stop leak if safe to do so. Store locked up. Dispose of contents/container in accordance with container supplier/owner instructions. Use a back flow preventive device in the piping. Do not open valve until connected to equipment prepared for use. Use only equipment of compatible materials of construction. Open valve slowly. Use only equipment cleaned for oxygen service. Always keep container in upright position. DO NOT change or force fit connections. Avoid spills. Do not walk on or roll equipment over spills. Read and follow the Matheson Tri-Gas Safety Data Sheet (SDS) before use.

FIRST AID: IF INHALED: Remove person to fresh air and keep comfortable for breathing. Call a POSION CENTER or doctor/physician if you feel unwell.

IF ON SKIN: Thaw frosted parts with lukewarm water. Do not rub affected area. Get immediate medical advice/attention.

CAS: 10024-97-2

CONTAINER CONTENTS: LTRS: CU FT:

DO NOT REMOVE THIS PRODUCT LABEL.

WARNING: This product can expose you to chemicals including Nitrous Oxide, which is known to the State of California to cause birth defects or other reproductive harm. For more information go to www.P65Warnings.ca.gov.

MATHESON The Gas Professionals

MATHESON TRI-GAS

909 LAKE CAROLYN PKWY. SUITE 1300

IRVING, TEXAS 75039 . 1-800-416-2505